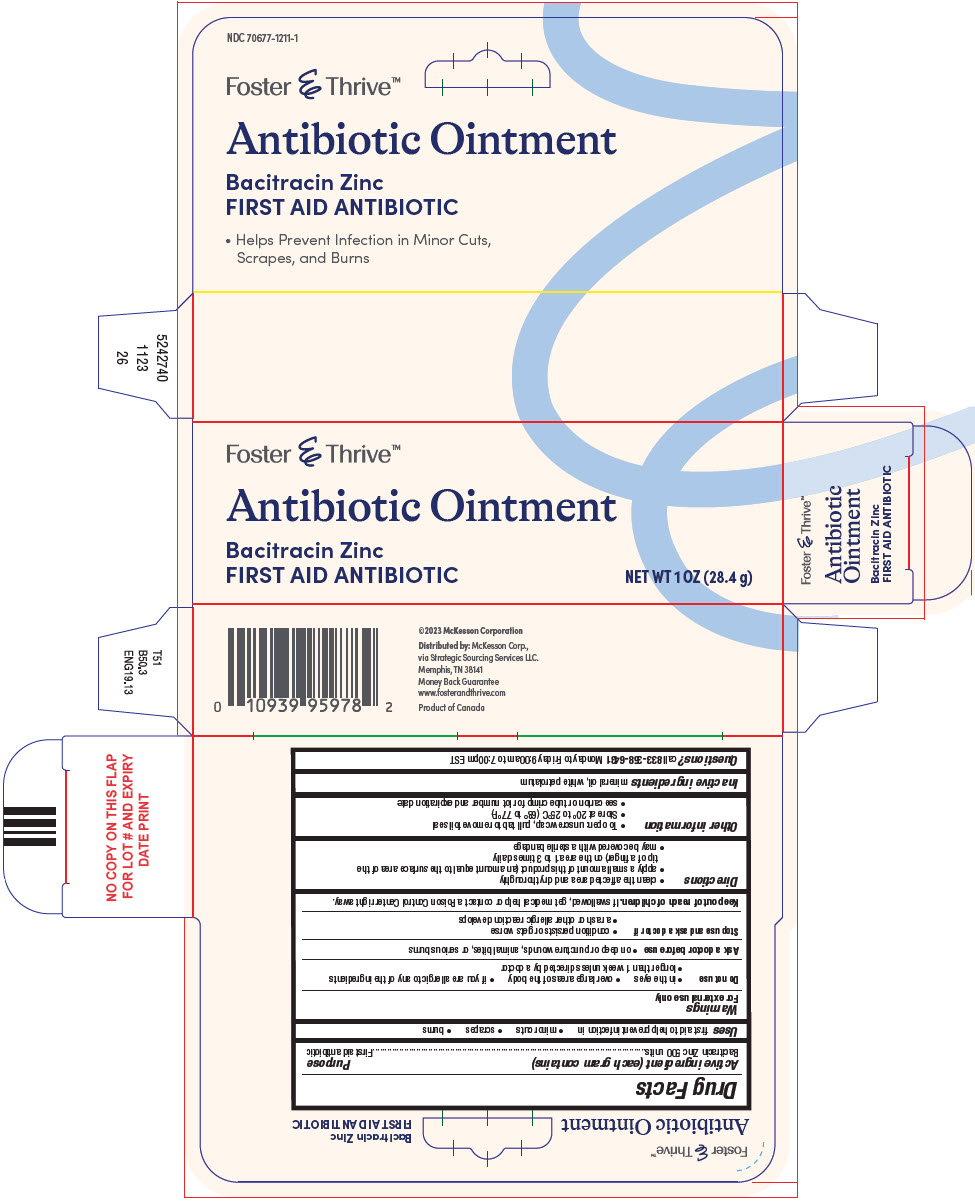 DRUG LABEL: Bacitracin Zinc
NDC: 70677-1211 | Form: OINTMENT
Manufacturer: STRATEGIC SOURCING SERVICES LLC
Category: otc | Type: HUMAN OTC DRUG LABEL
Date: 20250711

ACTIVE INGREDIENTS: BACITRACIN ZINC 500 [USP'U]/1 g
INACTIVE INGREDIENTS: MINERAL OIL; PETROLATUM

Bacitracin Zinc

Drug Facts

Active ingredient (each gram contains)

Bacitracin Zinc 500 units

Purpose

First aid antibiotic

Uses

first aid to help prevent infection in

- minor cuts
- scrapes
- burns

Warnings

For external use only

Do not use

- in the eyes
- over large areas of the body
- if you are allergic to any of the ingredients
- longer than 1 week unless directed by a doctor

Ask a doctor before use

- on deep or puncture wounds, animal bites, or serious burns

Stop use and ask a doctor if

- condition persists or gets worse
- a rash or other allergic reaction develops

Keep out of reach of children.If swallowed, get medical help or contact a Poison Control Center right away.

Directions

- clean the affected area and dry thoroughly
- apply a small amount of this product (an amount equal to the surface area of the tip of a finger) on the area 1 to 3 times daily
- may be covered with a sterile bandage

Other information

- To open: unscrew cap, pull tab to remove foil seal
- Store at 20° to 25°C (68° to 77°F)
- see carton or tube crimp for lot number and expiration date

Inactive ingredients

mineral oil, white petrolatum

Questions?

call 833-358-6431Monday to Friday 9:00am to 7:00pm EST

Distributed by:McKesson Corp.,
via Strategic Sourcing Services LLC.
Memphis, TN 38141

PRINCIPAL DISPLAY PANEL - 28.4 g Tube Carton

Foster & Thrive™

Antibiotic Ointment

Bacitracin Zinc
FIRST AID ANTIBIOTIC

NET WT 1 OZ (28.4 g)